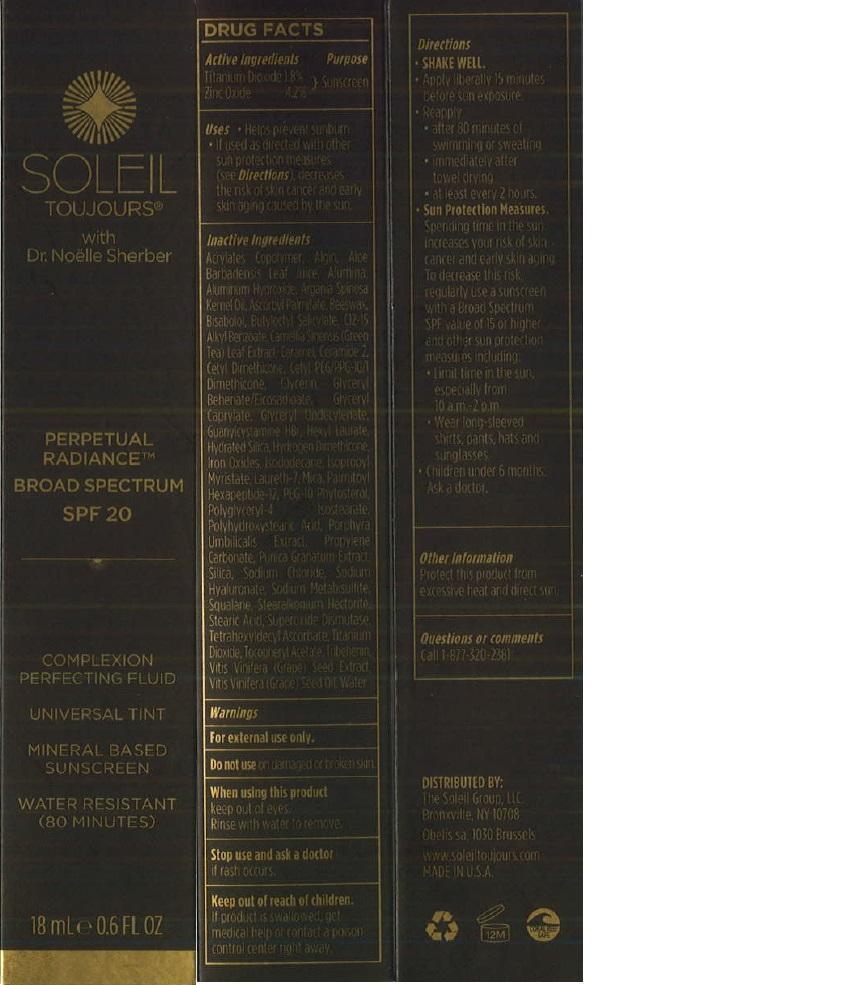 DRUG LABEL: Soleil Toujours
NDC: 58443-0185 | Form: LOTION
Manufacturer: Prime Enterprises, Inc.
Category: otc | Type: HUMAN OTC DRUG LABEL
Date: 20200117

ACTIVE INGREDIENTS: TITANIUM DIOXIDE 17.6 mg/1 mL; ZINC OXIDE 41.2 mg/1 mL
INACTIVE INGREDIENTS: BUTYLOCTYL SALICYLATE; ALUMINUM OXIDE; SILICON DIOXIDE; STEARIC ACID; 12-HYDROXYSTEARIC ACID; ALKYL (C12-15) BENZOATE; ISOPROPYL MYRISTATE; STEARALKONIUM HECTORITE; DIMETHICONE; GLYCERYL BEHENATE/EICOSADIOATE; PROPYLENE CARBONATE; ALOE VERA LEAF; ARGAN OIL; .ALPHA.-TOCOPHEROL ACETATE; LEVOMENOL; YELLOW WAX; TRIBEHENIN; CERAMIDE 2; .BETA.-SITOSTEROL; PALMITOYL HEXAPEPTIDE-12; CARAMEL; CETYL DIMETHICONE 150; CETYL PEG/PPG-10/1 DIMETHICONE (HLB 2); GLYCERIN; GLYCERYL CAPRYLATE; GLYCERYL MONOUNDECYLENATE; GUANYLCYSTAMINE HYDROBROMIDE; FERRIC OXIDE RED; ISODODECANE; LAURETH-7; MICA; POLYGLYCERYL-4 ISOSTEARATE; HEXYL LAURATE; SODIUM CHLORIDE; HYALURONATE SODIUM; SODIUM METABISULFITE; SQUALANE; ORGOTEIN; TETRAHEXYLDECYL ASCORBATE; CARBOMER INTERPOLYMER TYPE A (55000 CPS); HYDRATED SILICA; SODIUM ALGINATE; ALUMINUM HYDROXIDE; GRAPE SEED OIL; VITIS VINIFERA SEED; GREEN TEA LEAF; PORPHYRA UMBILICALIS; PUNICA GRANATUM ROOT BARK; WATER

Active ingredients

Titanium Dioxide 1.8 % and Zinc Oxide 4.2 %

Purpose

Sunscreen

Uses

- helps prevent sunburn
- If used as directed with other sun protection measures (see Directions), decreases the risk of skin cancer and early skin aging caused by the sun

Inactive Ingredients

Acrylates Copolymer, Algin, Aloe Barbadensis Leaf Juice, Alumina, Aluminum Hydroxide, Argania Spinosa Kernel Oil, Ascorbyl Palmitate, Beeswax, Bisabolol, Butyloctyl Salicylate, C12-15 Alkyl Benzoate, Camellia Sinensis (Green Tea) Leaf Extract, Caramel, Ceramide 2, Cetyl Dimethicone, Cetyl PEG/PPG-10/1 Dimethicone, Glycerin, Glyceryl Behenate/Eicosadioate, Glyceryl Caprylate, Glyceryl Undecylenate, Guanylcystamine HBr, Hexyl Laurate, Hydrated Silica, Hydrogen Dimethicone, Iron Oxides, Isododecane, Isopropyl Myristate, Laureth-7, Mica, Palmitoyl Hexapeptide-12, PEG-10 Phytosterol, Polyglyceryl-4 Isostearate, Polyhydroxystearic Acid, Porphyra Umbilicalis Extract, Propylene Carbonate, Punica Granatum Extract, Silica, Sodium Chloride, Sodium Hyaluronate, Sodium Metabisulfite, Squalane, Stearalkonium Hectorite, Stearic Acid, Superoxide Dismutase, Tetrahexyldecyl Ascorbate, Titanium Dioxide, Tocopheryl Acetate, Tribehenin, Vitis Vinifera (Grape) Seed Extract, Vitis Vinifera (Grape) Seed Oil, Water

Warnings

OTHER SAFETY INFORMATION

For external use only.

Do not use on damaged or broken skin.

When using this product

keep out of eyes.

Rinse with water to remove.

Stop use and ask a doctor

if rash occurs.

Keep out of reach of children.

If product is swallowed, get medical help or contact a poison control center right away.

Directions

- SHAKE WELL.
- Apply liberally 15 minutes before sun exposure
- Reapply:
- after 80 minutes of swimming or sweating
- immediately after towel drying
- at least every 2 hours
- Sun Protection Measures. Spending time in the sun increases your risk of skin cancer and early skin aging. To decrease this risk, regularly use a sunscreen with a broad spectrum SPF of 15 or higher and other sun protection measures including:
- Limit time in the sun, especially from 10 a.m. - 2 p.m.
- Wear long-sleeve shirts, pants, hats, and sunglasses
- Children under 6 months: Ask a doctor.

Other information

- Protect this product from excessive heat and direct sun.

Questions or comments

Call toll free 1-877-320-2381

PRINCIPAL DISPLAY PANEL - 18mL Tube with Applicator

SOLEIL

Toujours®

with

Dr. Noëlle Sherber

PERPETUAL

RADIANCE™

BROAD SPECTRUM

SPF 20

COMPLEXION

PERFECTING FLUID

UNIVERSAL TINT

MINERAL BASED

SUNSCREEN

WATER RESISTANT

(80 MINUTES)

18 mL e 0.6 FL OZ